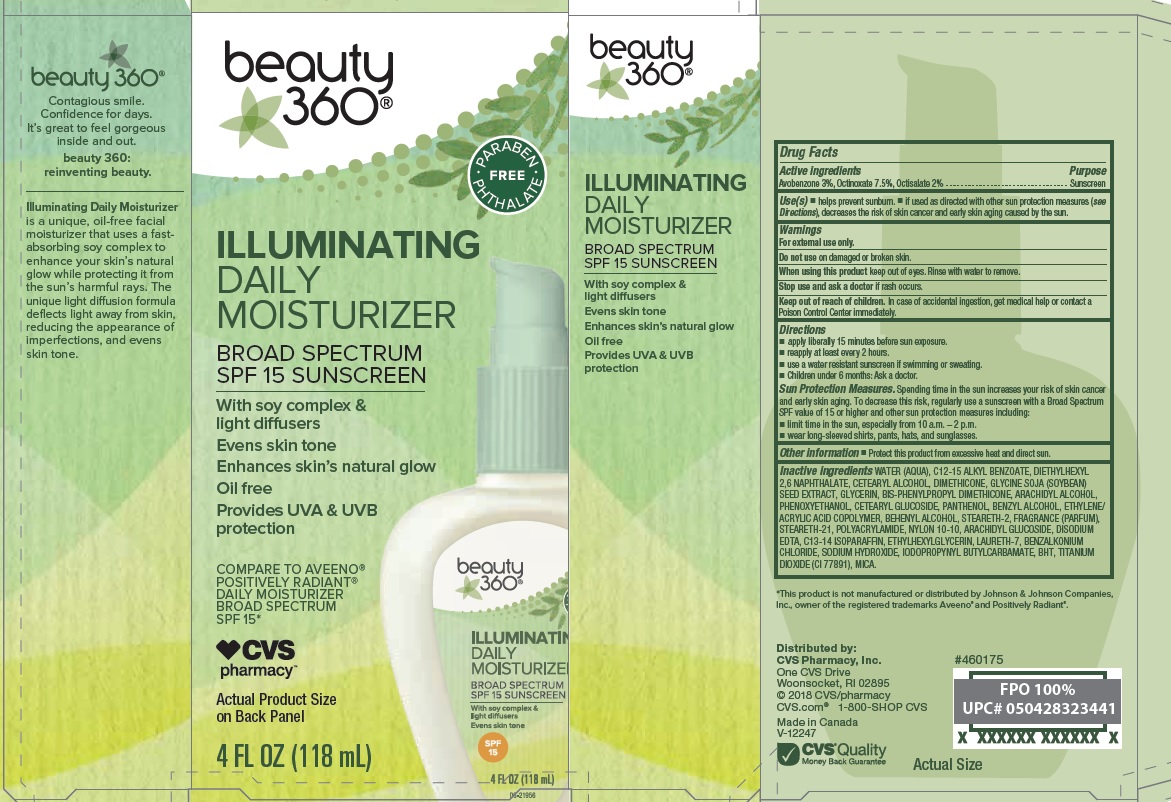 DRUG LABEL: Illuminating Daily Moisturizer SPF 15
NDC: 59779-601 | Form: LOTION
Manufacturer: CVS Pharmacy
Category: otc | Type: HUMAN OTC DRUG LABEL
Date: 20180416

ACTIVE INGREDIENTS: AVOBENZONE 30 mg/1 mL; OCTINOXATE 75 mg/1 mL; OCTISALATE 20 mg/1 mL
INACTIVE INGREDIENTS: WATER; ALKYL (C12-15) BENZOATE; DIETHYLHEXYL 2,6-NAPHTHALATE; CETOSTEARYL ALCOHOL; DIMETHICONE; SOYBEAN; GLYCERIN; BIS-PHENYLPROPYL DIMETHICONE (15 CST); ARACHIDYL ALCOHOL; PHENOXYETHANOL; CETEARYL GLUCOSIDE; PANTHENOL; BENZYL ALCOHOL; ACRYLIC ACID/ETHYLENE COPOLYMER (600 MPA.S); DOCOSANOL; STEARETH-2; STEARETH-21; POLYACRYLAMIDE (10000 MW); NYLON-12; ARACHIDYL GLUCOSIDE; EDETATE DISODIUM; C13-14 ISOPARAFFIN; ETHYLHEXYLGLYCERIN; LAURETH-7; BENZALKONIUM CHLORIDE; SODIUM HYDROXIDE; IODOPROPYNYL BUTYLCARBAMATE; BUTYLATED HYDROXYTOLUENE; TITANIUM DIOXIDE; MICA

Drug Facts

Active ingredients

Avobenzone 3%, Octinoxate 7.5%, Octisalate 2%

Purpose

Sunscreen

Use(s)

- helps prevent sunburn.
- if used as directed with other sun protection measures (see Directions), decreases the risk of skin cancer and early skin aging caused by the sun.

Warnings

For external use only.

Do not use

on damaged or broken skin.

When using this product

keep out of eyes. Rinse with water to remove.

Stop use and ask a doctor if

rash occurs.

Keep out of reach of children.

In case of accidental ingestion, get medical help or contact a Poison Control Center immediately.

Directions

- apply liberally 15 minutes before sun exposure.
- reapply at least every 2 hours.
- use a water resistant sunscreen if swimming or sweating.
- Children under 6 months: Ask a doctor.

Sun Protection Measures. Spending time in the sun increases your risk of skin cancer and early skin aging. To decrease this risk, regularly use a sunscreen with a Broad Spectrum SPF value of 15 or higher and other sun protection measures including:

- limit time in the sun, especially from 10 a.m. - 2 p.m.
- wear long-sleeved shirts, pants, hats, and sunglasses.

Other information

- protect this product from excessive heat and direct sun.

Inactive ingredients

Water (Aqua), C12-15 Alkyl Benzoate, Diethylhexyl 2,6 Naphthalate, Cetearyl Alcohol, Dimethicone, Glycine Soja (Soybean) Seed Extract, Glyceirn, BIS-Phenylpropyl Dimethicone, Arachidyl Alcohol, Phenoxyethanol, Cetearyl Glucoside, Panthenol, Benzyl Alcohol, Ethylene/Acrylic Acid Copolymer, Behenyl Alcohol, Steareth-2, Fragrance (Parfum), Steareth-12, Polyacrylamide, Nylon 10-10, Arachidyl Glucoside, Disodium EDTA, C13-14 Isoparaffin, Ethylhexylglycerin, Laureth-7, Benzalkonium Chloride, Sodium Hydroxide, Iodopropynyl Butylcarbamate, BHT, Titanium Dioxide (CI 77891), Mica.